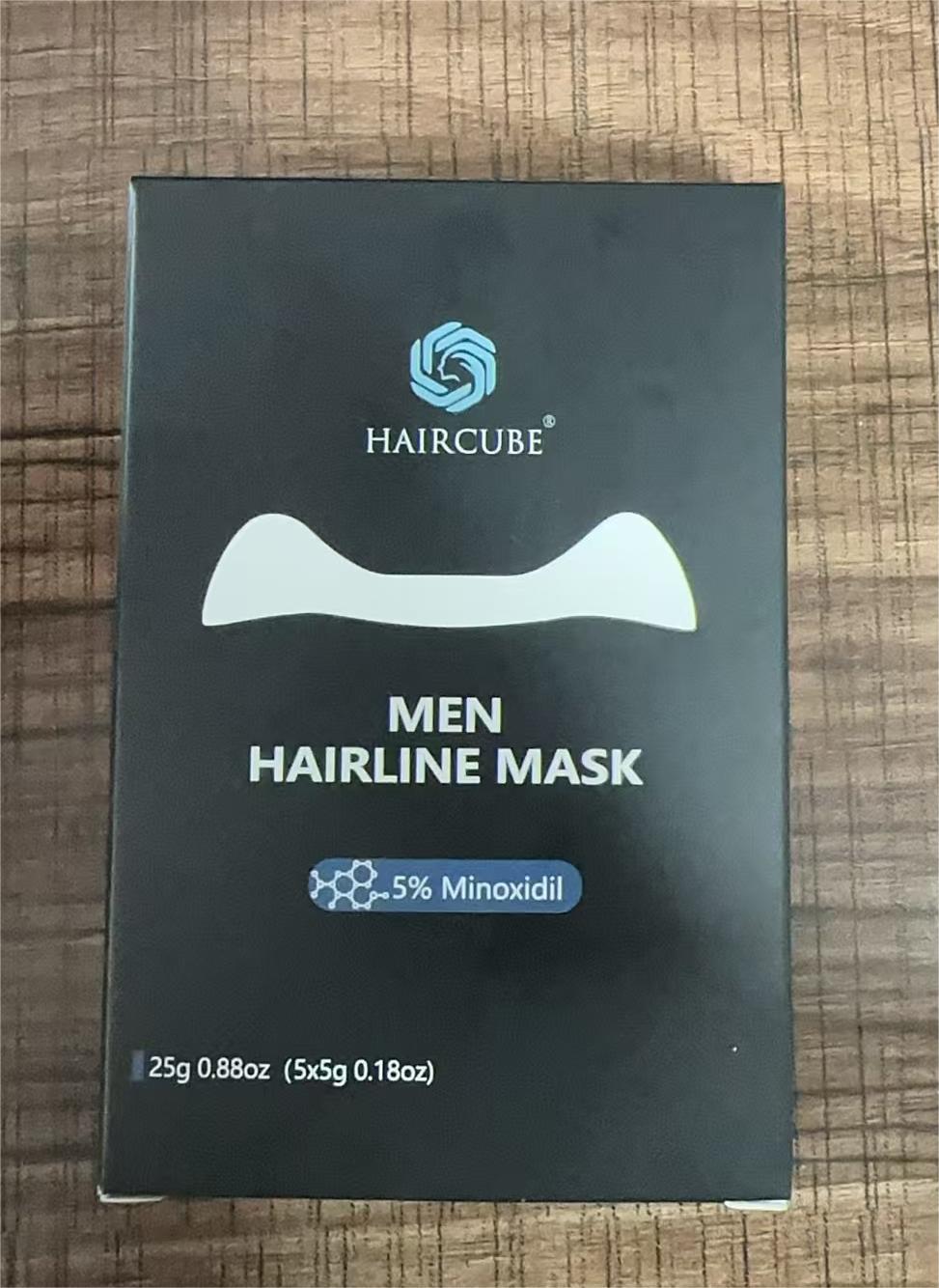 DRUG LABEL: MEN HAIRLINE MASK
NDC: 84979-020 | Form: PASTE
Manufacturer: Guangdong Dazhan Biomedical Technology Co., Ltd
Category: otc | Type: HUMAN OTC DRUG LABEL
Date: 20241122

ACTIVE INGREDIENTS: MINOXIDIL 1.25 g/1.25 g
INACTIVE INGREDIENTS: GLYCERIN; PANTHENOL; CAFFEINE; BIOTINOYL TRIPEPTIDE-1; APIGENIN; BUTYLENE GLYCOL; BIOTIN; NIACINAMIDE; BORNEOL; IODOPROPYNYL BUTYLCARBAMATE; POLYSORBATE 20; OLEANOLIC ACID; PEG-40 HYDROGENATED CASTOR OIL; WATER; AZELAIC ACID

INDICATIONS AND USAGE

This product is intended to promote hair regrowth and reduce hair thinning along the hairline.

STOP USE

You experience redness, swelling, irritation, or pain at the application site.
Unusual hair loss occurs.
You develop a rash or severe irritation that does not go away.
You experience dizziness, faintness, or headache after application.
Signs of an allergic reaction, such as hives, itching, or difficulty breathing, occur.
No improvement is seen after consistent use for the specified duration (e.g., 4 months).

DOSAGE AND ADMINISTRATION

Clean the hairline with water and dry it
Take out the middle layer of the mask and stick it on the hairline
Gently massage with your fingertips to spread the liquid evenlyRemove the mask after 10-15minutes,rinse thoroughly .it is recommended to use once daily

INACTIVE INGREDIENT

WATER

GLYCERIN

PANTHENOL

NIACINAMIDE

BIOTA ORIENTALIS LEAF EXTRACT

IODOPROPYNYL BUTYLCARBAMATE

POLYSORBATE 20

CAFFEINE

PROPYLENE GLYCOL

AZELAIC ACID

BUTYLENE GLYCOL

PEG-40 HYDROGENATED CASTOR OIL

MENTHA HAPLOCALIX EXTRACT

BORNEOL

AROMA

DISODIUM EDTA

APIGENIN

ACETYL TETRAPEPTIDE-3

BIOTIN

OLEANOLIC ACID

BIOTINOYL TRIPEPTIDE-1

PURPOSE

Hair Regrowth Treatment

Helps to promote hair regrowth and prevent further hair loss.

KEEP OUT OF REACH OF CHILDREN

If swallowed, get medical help or contact a Poison Control Center right away.

WARNINGS

Avoid contact with eyes. If contact occurs, rinse thoroughly with water.
Keep out of reach of children.
For external use only.
Perform a patch test before use. Discontinue if irritation occurs